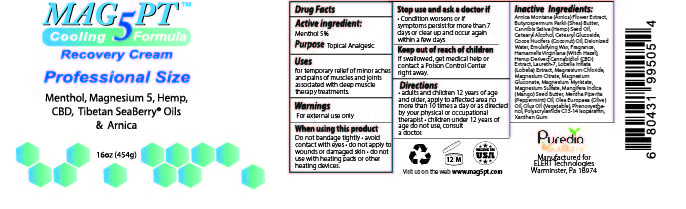 DRUG LABEL: Mag 5 PT Cooling Formula Recovery Cream
NDC: 76348-510 | Form: CREAM
Manufacturer: RENU LABORATORIES, LLC
Category: otc | Type: HUMAN OTC DRUG LABEL
Date: 20251118

ACTIVE INGREDIENTS: MENTHOL 22.7 g/454 g
INACTIVE INGREDIENTS: MAGNESIUM OROTATE; MAGNESIUM GLUCONATE; HIPPOPHAE RHAMNOIDES SEED OIL; WITCH HAZEL; NIACINAMIDE; CETEARYL GLUCOSIDE; PEG-100 STEARATE; OLIVE OIL; CANNABIS SATIVA SEED OIL; PHENOXYETHANOL; SHEA BUTTER; PEPPERMINT OIL; MAGNESIUM SULFATE, UNSPECIFIED; CORN OIL; POLYACRYLAMIDE (10000 MW); LAURETH-7; MAGNESIUM CHLORIDE; C13-14 ISOPARAFFIN; CANNABIDIOL; CETOSTEARYL ALCOHOL; WHITE WAX; ARNICA MONTANA FLOWER; WATER; GLYCERYL MONOSTEARATE; LOBELIA INFLATA LEAF; STEARIC ACID; COCONUT OIL; MAGNESIUM MYRISTATE; HIPPOPHAE RHAMNOIDES FRUIT OIL; MANGIFERA INDICA SEED BUTTER

MAG 5 PT COOLING FORMULA RECOVERY CREAM

ACTIVE INGREDIENT

Menthol 5%

PURPOSE

Topical Analgesic

WARNINGS

For external use only

WHEN USING

Do not bandage tightly

avoid contact with eyes

do not apply to wounds or damaged skin

do not use with heating pads or other heatng devices

Stop use and ask a doctor if Condition worsens or if symptoms persist for more than 7 days or clear up and occur again within a few days.

KEEP OUT OF REACH OF CHILDREN

If swallowed, get medical help or contact a Poison Control Center right away.

DOSAGE AND ADMINISTRATION

Directions Adults and children 12 years of age and older, apply to affected area no more than three times a day or as directed by your physical or occupational therapist

- children under 12 years of age: consult your physical or occupational therapist.

INACTIVE INGREDIENT

Arnica Montana (Arnica) Flower Extract, Butyrospermum Parkii (Shea Butter), Cannabis Sativa (Hemp) Seed Oil and Hemp-Derived Cannabidiol (CBD) Extract, Cetearyl Alcohol, Cetearyl Glucoside, Citrus Paradisi (Grapefruit) Extract, Cocos Nucifera (Coconut) Oil, C13-14 Isoparaffin, Deionized Water, Emulsifying Wax, Hamamelis Virginiana (Witch Hazel), Hippophae Rhamnoides (Sea Berry) Fruit Oil, Hippophae Rhamnoides (Sea Berry) Seed Oil, Laureth-7, Lobelia Flower Extract, Magnesium Chloride, Magnesium Gluconate, Magnesium Myristate, Magnesium Orotate, Magnesium Sulfate, Mangifera Indica (Mango) Seed Butter, Mentha piperita (Peppermint) Leaf Oil, Olea Europaea (Olive) Oil, Olus Oil (vegetable), Phenoxyethanol, Polyacrylamide, Xanthan Gum

QUESTIONS

Visit us on the web www.mag5pt.com

INDICATIONS AND USAGE

For temporary relief of minor aches and pains of muscles and joints associated with deep muscle therapy treatments.